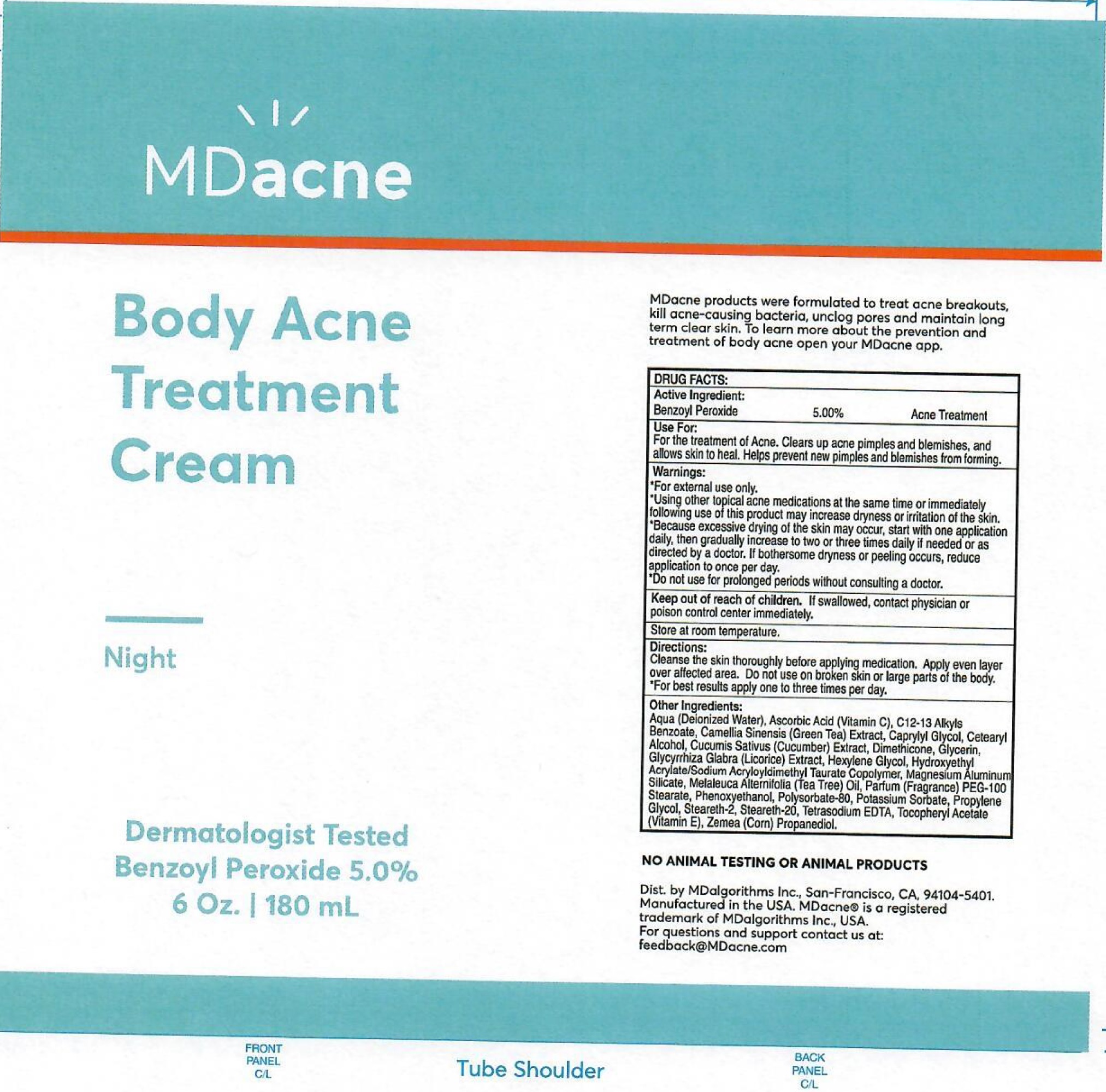 DRUG LABEL: MD-Acne Body Acne Treatment
NDC: 71804-230 | Form: CREAM
Manufacturer: MD Algorithms Inc.
Category: otc | Type: HUMAN OTC DRUG LABEL
Date: 20231111

ACTIVE INGREDIENTS: BENZOYL PEROXIDE 50 mg/1 mL
INACTIVE INGREDIENTS: WATER; ASCORBIC ACID; ALKYL (C12-15) BENZOATE; GREEN TEA LEAF; CAPRYLYL GLYCOL; CETOSTEARYL ALCOHOL; CUCUMBER; DIMETHICONE; GLYCERIN; GLYCYRRHIZA GLABRA; HEXYLENE GLYCOL; HYDROXYETHYL ACRYLATE/SODIUM ACRYLOYLDIMETHYL TAURATE COPOLYMER (100000 MPA.S AT 1.5%); MAGNESIUM ALUMINUM SILICATE; TEA TREE OIL; PEG-100 STEARATE; PHENOXYETHANOL; POLYSORBATE 80; POTASSIUM SORBATE; PROPYLENE GLYCOL; STEARETH-2; STEARETH-20; EDETATE SODIUM; .ALPHA.-TOCOPHEROL ACETATE; CORN

MD-Acne Body Acne Treatment Cream

Active Ingredient:

Benzoyl Peroxide 5.00%

PURPOSE

Acne Treatment

Use For:

For the treatment of Acne. Clears up acne pimples and blemishes, and allows skin to heal. Helps prevent new pimples and blemishes from forming.

Warnings:

- For external use only.
- Using other topical acne medications the same time or immerdiately following use of this product may increase dryness or irritation of the skin.
- Because excessive drying of the skin may occur, start with one application daily, then gradually increase to two or three times daily if needed or as directed by a doctor. If bothersome dryness or peeling occurs, reduce application to once per day.

Do not use

- for prolonged periods without consulting a doctor.

Keep out of reach of children.

If swallowed, contact physician or poison control center immediately.

Store at room temperature

Directions:

Cleanse the skin thoroughly before applying medication. Apply even layer over affected area. Do not use on broken skin or large parts of the body.

- For best results apply one to three times per day.

Other Ingredients:

Aqua (Deionized Water), Ascorbic Acid (vitamin C), C12-15 Alkyl Benzoate, Camellia Sinensis (Green Tea) Extract, Caprylyl Glycol, Cetearyl Alcohol, Cucumis Sativus (Cucumber) Extract, Dimethicone, Glycerin, Glycyrrhiza Glabra (Licorice) Extract, Hexylene Glycol, Hydroxyethyl Acrylate/Sodium Acryloyldimethyl Taurate Copolymer, Magnesium Aluminum Silicate, Melaleuca Alternifolia (Tea Tree) Oil, Parfum (Fragrance), PEG 100 Stearate, Phenoxyethanol, Polysorbate-80, Potassium Sorbate, Propylene Glycol, Steareth-2, Steareth-20, Tetrasodium EDTA, Tocopheryl Acetate (Vitamin E), Zemea (Corn) Propanediol.